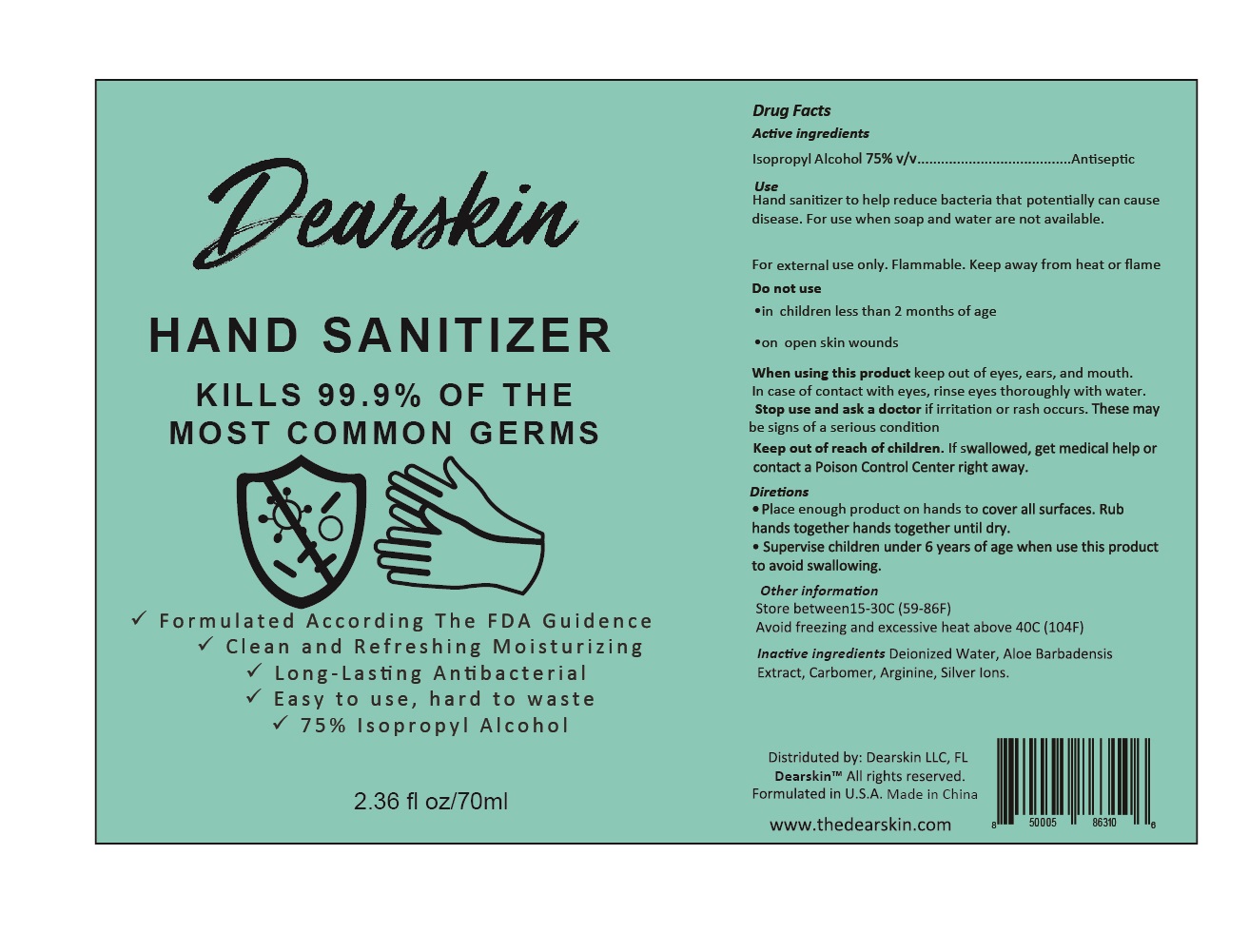 DRUG LABEL: Hand Sanitizer
NDC: 90067-001 | Form: GEL
Manufacturer: Guangzhou Mebamy Cosmetics Co., Ltd.
Category: otc | Type: HUMAN OTC DRUG LABEL
Date: 20200809

ACTIVE INGREDIENTS: ISOPROPYL ALCOHOL 75 mL/100 mL
INACTIVE INGREDIENTS: ARGININE; ALOE VERA LEAF; CARBOMER HOMOPOLYMER, UNSPECIFIED TYPE; WATER; SILVER CATION

90067-001 Hand Sanitizer

Active Ingredient(s)

Isopropyl Alcohol 75%v/v

Purpose

Antiseptic

Use

Hand sanitizer to help reduce bacteria that potentially can cause disease. For use when soap and water are not available.
For external use only. Flammable. Keep away from heat or flame

Warnings

/

Do not use

in children less than 2 months of age
on open skin wounds

WHEN USING

In case of contact with eyes, rinse eyes thoroughly with water
Stop use and ask a doctor if irritation or rash occurs. These may be signs of a serious condition

Stop use and ask a doctor if irritation or rash occurs. These may be signs of a serious condition.

Keep out of reach of children. If swallowed, get medical help or contact a Poison Control Center right away.

Directions

Place enough product on hands to cover all surfaces. Rub hands together hands together until dry
Supervise children under 6 years of age when use this product to avoid swallowing

Other information

Store between 15-30C (59-86F)
Avoid freezing and excessive heat above 40C(104F)

Inactive ingredients

Deionized Water, Aloe Barbadensis Extract, Carbomer, Arginine, Silver Ions